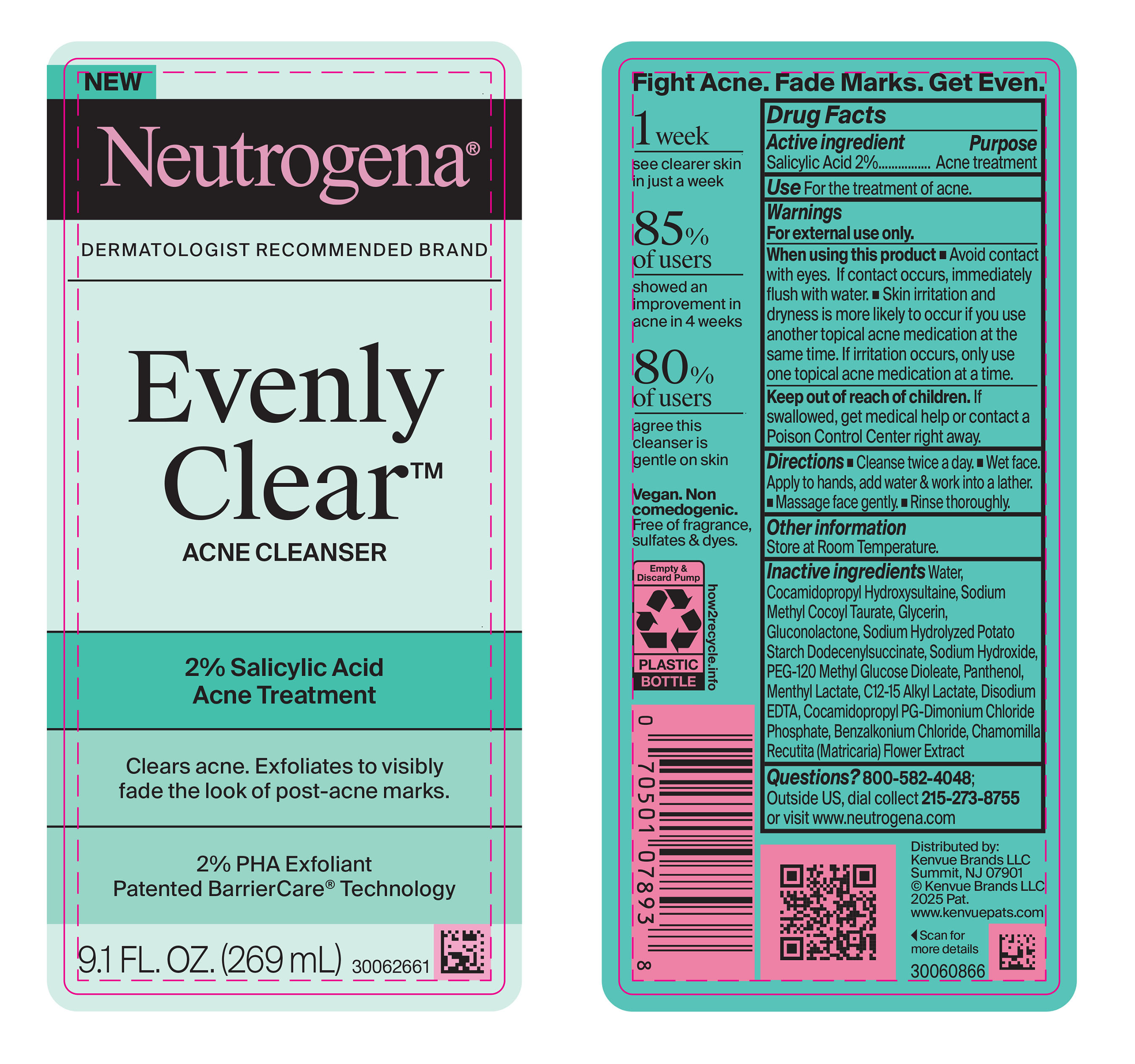 DRUG LABEL: Neutrogena Evenly Clear Acne Cleanser
NDC: 69968-0942 | Form: LIQUID
Manufacturer: Kenvue Brands LLC
Category: otc | Type: HUMAN OTC DRUG LABEL
Date: 20260122

ACTIVE INGREDIENTS: SALICYLIC ACID 20 mg/1 mL
INACTIVE INGREDIENTS: PANTHENOL; BENZALKONIUM CHLORIDE; COCAMIDOPROPYL HYDROXYSULTAINE; SODIUM HYDROLYZED POTATO STARCH DODECENYLSUCCINATE; WATER; SODIUM METHYL COCOYL TAURATE; EDETATE DISODIUM; SODIUM HYDROXIDE; GLYCERIN; COCAMIDOPROPYL PG-DIMONIUM CHLORIDE PHOSPHATE; C12-15 ALKYL LACTATE; PEG-120 METHYL GLUCOSE DIOLEATE; CHAMOMILE; MENTHYL LACTATE; GLUCONOLACTONE

Neutrogena Evenly Clear Acne Cleanser

Drug Facts

ACTIVE INGREDIENT

Salicylic Acid (2%)

PURPOSE

Acne treatment

Uses

For the treatment of acne.

Warnings

- For external use only

When using this product ▪ Avoid contact with eyes. If contact occurs, immediately flush with water ▪ Skin irritation and dryness is more likely to occur if you use another topical acne medication at the same time. If irritation occurs, only use one topical acne medication at a time.

Keep out of reach of children. If swallowed, get medical help or contact a Poison Control Center right away.

Directions

▪ Cleanse twice a day ▪ Wet face. Apply to hands, add water & work into a lather.▪ Massage face gently. ▪ Rinse thoroughly

Other information

Store at Room Temperature.

Inactive ingredients

Water, Cocamidopropyl Hydroxysultaine, Sodium Methyl Cocoyl Taurate, Glycerin, Gluconolactone, Sodium Hydrolyzed Potato Starch Dodecenylsuccinate, Sodium Hydroxide, PEG-120 Methyl Glucose Dioleate, Panthenol, Menthyl Lactate, C12-15 Alkyl Lactate, Disodium EDTA, Cocamidopropyl PG-Dimonium Chloride Phosphate, Benzalkonium Chloride, Chamomilla Recutita (Matricaria) Flower Extract

Questions?

800-582-4048 Outside US, dial collect 215-273-8755 or visit www.neutrogena.com

Distributed by:

Kenvue Brands LLC
Summit, NJ 07901

PRINCIPAL DISPLAY PANEL - 269 mL Bottle Label

NEW

Neutrogena®

DERMATOLOGIST RECOMMENDED BRAND

Evenly

Clear™

ACNE CLEANSER

2% Salicylic Acid

Acne Treatment

Clears acne. Exfoliates to visibly

fade the look of post-acne marks.

2% PHA Exfoliant

Patented BarrierCare®Technology

9.1 FL.OZ. (269 mL)